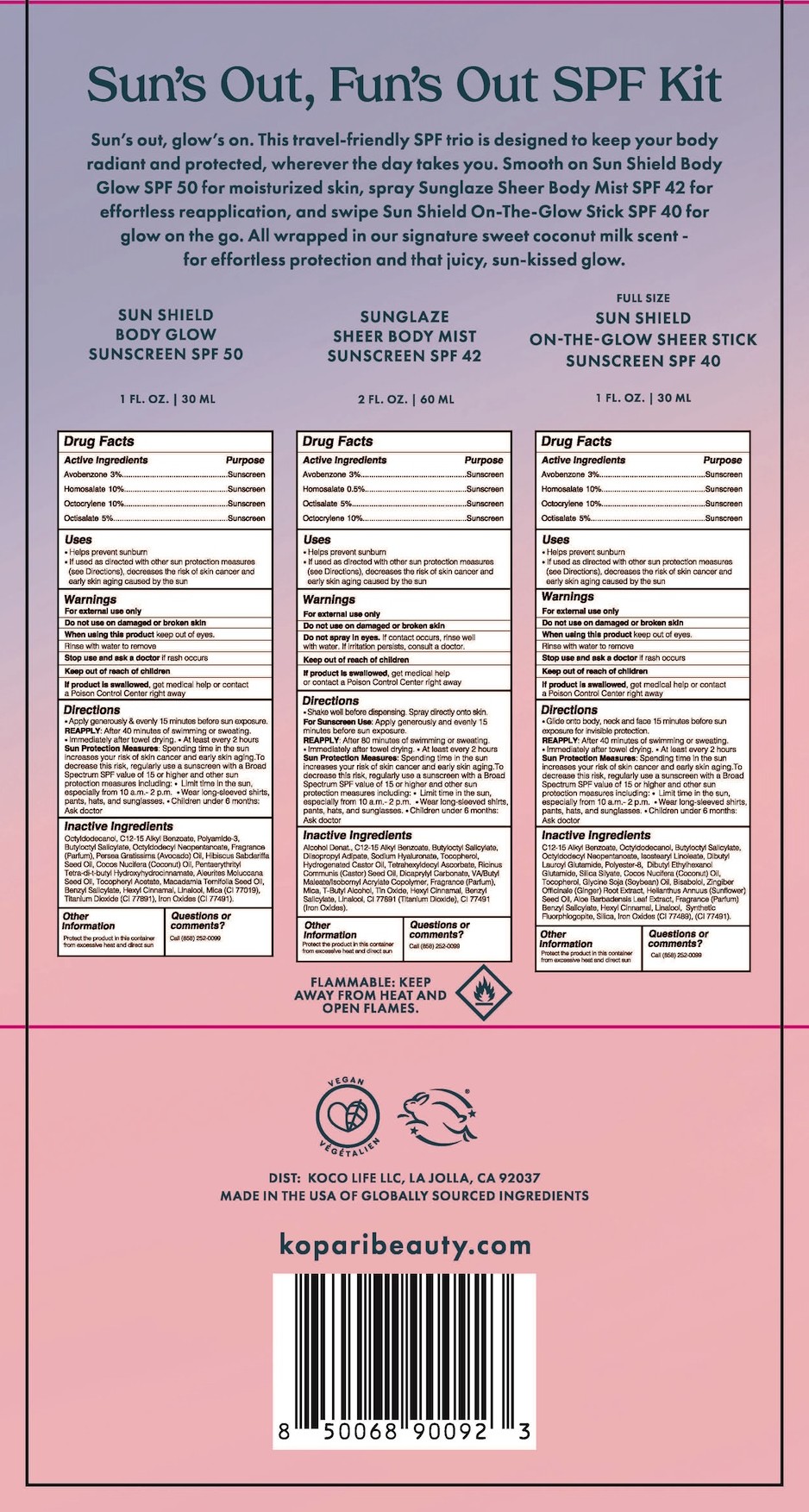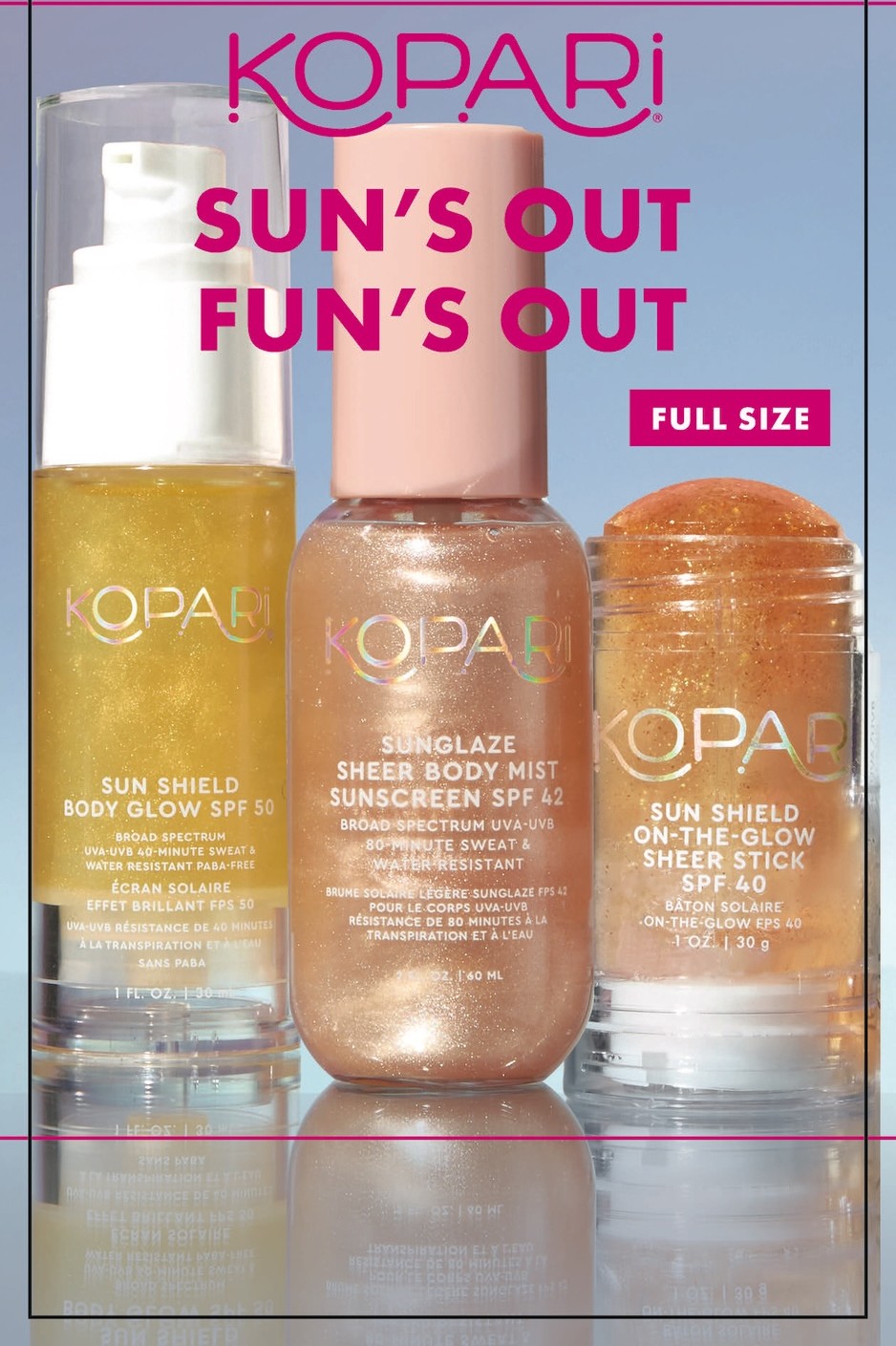 DRUG LABEL: Suns Out Funs Out
NDC: 84130-024 | Form: KIT | Route: TOPICAL
Manufacturer: Koco Life LLC
Category: otc | Type: HUMAN OTC DRUG LABEL
Date: 20251215

ACTIVE INGREDIENTS: OCTOCRYLENE 10 g/100 g; HOMOSALATE 10 g/100 g; AVOBENZONE 3 g/100 g; OCTISALATE 5 g/100 g; AVOBENZONE 30 mg/1 mL; HOMOSALATE 5 mg/1 mL; OCTISALATE 50 mg/1 mL; OCTOCRYLENE 100 mg/1 mL; OCTOCRYLENE 100 mg/1 mL; AVOBENZONE 30 mg/1 mL; HOMOSALATE 100 mg/1 mL; OCTISALATE 50 mg/1 mL
INACTIVE INGREDIENTS: CITRAL; .ALPHA.-HEXYLCINNAMALDEHYDE; DIBUTYL ETHYLHEXANOYL GLUTAMIDE; BENZYL SALICYLATE; OCTYLDODECYL NEOPENTANOATE; FERRIC OXIDE RED; LINALOOL, (+)-; ALKYL (C12-15) BENZOATE; SUNFLOWER OIL; GINGER; ISOSTEARYL LINOLEATE; SOYBEAN OIL; TOCOPHEROL; COCONUT OIL; MAGNESIUM POTASSIUM ALUMINOSILICATE FLUORIDE; POLYESTER-8 (1400 MW, CYANODIPHENYLPROPENOYL CAPPED); BUTYLOCTYL SALICYLATE; LEVOMENOL; SILICON DIOXIDE; FARNESOL; DIBUTYL LAUROYL GLUTAMIDE; OCTYLDODECANOL; ALOE VERA LEAF; TERT-BUTYL ALCOHOL; BENZYL SALICYLATE; LINALOOL, (+/-)-; DIISOPROPYL ADIPATE; HYDROGENATED CASTOR OIL; ALKYL (C12-15) BENZOATE; HYALURONATE SODIUM; CASTOR OIL; ALCOHOL; DICAPRYLYL CARBONATE; BUTYLOCTYL SALICYLATE; TOCOPHEROL; TETRAHEXYLDECYL ASCORBATE; DIBUTYL MALEATE; FERRIC OXIDE RED; STANNIC OXIDE; .ALPHA.-HEXYLCINNAMALDEHYDE; TITANIUM DIOXIDE; MICA; BENZYL SALICYLATE; AVOCADO OIL; HIBISCUS SABDARIFFA SEED OIL; KUKUI NUT OIL; .ALPHA.-HEXYLCINNAMALDEHYDE; LINALOOL, (+/-)-; COCONUT OIL; OCTYLDODECYL NEOPENTANOATE; ALKYL (C12-15) BENZOATE; MICA; BUTYLOCTYL SALICYLATE; MACADAMIA OIL; .ALPHA.-TOCOPHEROL ACETATE; FERRIC OXIDE RED; OCTYLDODECANOL; POLYAMIDE-3 (12000 MW); TITANIUM DIOXIDE; PENTAERYTHRITOL TETRAKIS(3-(3,5-DI-TERT-BUTYL-4-HYDROXYPHENYL)PROPIONATE)

Sun's Out, Fun's Out Kit

84130-001-10 Sun Shield Body Glow SPF50 DX

Active ingredients

Avobenzone 3%

Homosalate 10%

Octocrylene 10%

Octisalate 5%

Purpose

Avobenzone 3% .........................Sunscreen

Homosalate 10%.........................Sunscreen

Octocrylene 10% ........................Sunscreen

Octisalate 5% .............................Sunscreen

Uses

• Helps prevent sunburn

• If used as directed with other sunprotection measures (see Directions),decreases the risk of skin cancer and earlyskin aging caused by the sun

Warnings

For external use only

Do not use on damaged or broken skin

When using this product keep out of eyes. Rinse with water to remove.

Stop use and ask a doctor if rash occurs

Keep out of reach of children. If product is swallowed, get medical help or contact a Poison Control Center right away.

Directions

• Apply generously & evenly 15 minutesbefore sun exposure.

REAPPLY: After 40 minutes of swimming or sweating. • Immediately after towel drying.• At least every 2 hours

Sun Protection Measures: Spending time in the sun increases your risk of skin cancer and early skin aging. To decrease this risk, regularly use a sunscreen with a Broad Spectrum SPF value of 15 or higher and other sun protection measures including: • Limit time in the sun, especially from 10 a.m.- 2 p.m. • Wear long-sleeved shirts, pants, hats, and sunglasses • Children under 6 months: Ask a doctor

Inactive ingredients

Octyldodecanol, C12-15 Alkyl Benzoate, Polyamide-3, Butyloctyl Salicylate, Octyldodecyl Neopentanoate, Fragrance (Parfum), Persea Gratissima (Avocado) Oil, Hibiscus Sabdariffa Seed Oil, Cocos Nucifera (Coconut) Oil, Pentaerythrityl Tetra-di-t-butyl Hydroxyhydrocinnamate, Aleurites Moluccana Seed Oil, Tocopheryl Acetate, Macadamia Ternifolia Seed Oil, Benzyl Salicylate, Hexyl Cinnamal, Linalool, Mica (CI 77019), Titanium Dioxide (CI 77891), Iron Oxides (CI 77491)

Other information

Protect the product in this container from excessive heat and direct sun

Questions or comments?

Call (858) 252-0099

84130-000-20 Sunglaze Sheer Body Mist Sunscreen SPF 42

Active ingredients

Avobenzone 3 %
Homosalate 0.5 %
Octisalate 5%
Octocrylene 10%

Purpose

Avobenzone 3 %....................Sunscreen
Homosalate 0.5 %....................Sunscreen
Octisalate 5%....................Sunscreen
Octocrylene 10%....................Sunscreen

Uses

- Helps prevent sunburn
- If used as directed with other sun protection measures (see Directions), decreases the risk of skin cancer & early skin aging caused by the sun.

Warnings

For external use only

Do not use on damaged or broken skin

Do not spray in eyes. If contact occurs, rinse well with water. If irritation persists, consult a doctor.

Keep out of reach of children.

If product is swallowed, get medical help or contact a Poison Control Center right away.

Directions

- Shake well before dispensing. Spray directly onto skin. For Sunscreen use:Apply generously and evenly 15 minutes before sun exposure. Reapply
- After 80 minutes of swimming or sweating. Immediately after towel drying.
- At least every 2 hours

Sun Protection Measures:

Spending time in the sun increases your

risk of skin cancer & early skin aging. To decrease this risk, regularly use a

sunscreen with a Broad Spectrum SPF value of 15 or higher & other sun

protection measures including:

- Limit time in the sun, especially from 10 a.m. - 2 p.m
- Wear long-sleeved shirts, pants, hats and sunglasses
- Children under 6 months: Ask a doctor

Inactive ingredients

Alcohol Denat., C12-15 Alkyl Benzoate, Butyloctyl Salicylate, Diisopropyl Adipate, Sodium Hyaluronate, Tocopherol, Hydrogenated Castor Oil, Tetrahexyldecyl Ascorbate, Ricinus Communis (Castor) Seed Oil, Dicaprylyl Carbonate, VA/Butyl Maleate/Isobornyl Acrylate Copolymer, Fragrance (Parfum), Mica, T-Butyl Alcohol, Tin Oxide, Hexyl Cinnamal, Benzyl Salicylate, Linalool, CI 77891 (Titanium Dioxide), CI 77491 (Iron Oxides)

Other information

Protect the product in this container from excessive heat and direct sun

QUESTIONS

Call (858) 252-0099

84130-004-10 Sun Shield On-the-Glow Sheer Stick SPF40

Active ingredients

Avobenzone 3%, Homosalate 10%, Octocrylene 10%, Octisalate 5%

Purpose

Avobenzone 3%, Homosalate 10%, Octocrylene 10%, Octisalate 5%...................Sunscreen

Uses

• Helps prevent sunburn • If used as directed with other sun protection measures (see Directions), decreases the risk of skin cancer & early skin aging caused by the sun

Warnings

For external use only

Do not use on damaged or broken skin

When using this product keep out of eyes. Rinse with water to remove.

Stop use and ask a doctor if rash occurs

Keep out of reach of children. If product is swallowed, get medical help or contact a Poison Control Center right away.

Directions

• Glide onto body, neck and face 15 minutesbefore sun exposure for invisible protection.

Reapply: After 40 minutes of swimming or sweating. •Immediately after towel drying. • At least every 2 hours

Sun Protection Measures: Spending time in the sun increases your risk of skin cancer & early skin aging. To decrease this risk, regularly use a sunscreen with a Broad Spectrum SPF value of 15 or higher & other sun protection measures including:• Limit time in the sun, especially from 10 a.m. - 2 p.m• Wear long-sleeved shirts, pants, hats and sunglasses• Children under 6 months: Ask a doctor

Inactive ingredients

C12-15 Alkyl Benzoate, Octyldodecanol, Butyloctyl Salicylate, Octyldodecyl Neopentanoate, Isostearyl Linoleate, Dibutyl Lauroyl Glutamide, Polyester-8, Dibutyl Ethylhexanoyl Glutamide, Silica Silylate, Zingiber Officinale (Ginger) Root Extract, Tocopherol, Cocos Nucifera (Coconut) Oil, Helianthus Annuus (Sunflower) Seed Oil, Aloe Barbadensis Leaf Extract, Glycine Soja (Soybean) Oil, Bisabolol, Fragrance (Parfum), Synthetic Fluorphlogopite, Silica, Hexyl Cinnamal, Benzyl Salicylate, Linalool, Farnesol, Citral, CI 77491 (Iron Oxides)

Other information

Protect the product in this container from excessive heat and direct sun

Questions/Comments

Call (858) 252-0099

PACKAGE LABEL

Kopari

Sun's Out

Fun's Out

Full Size